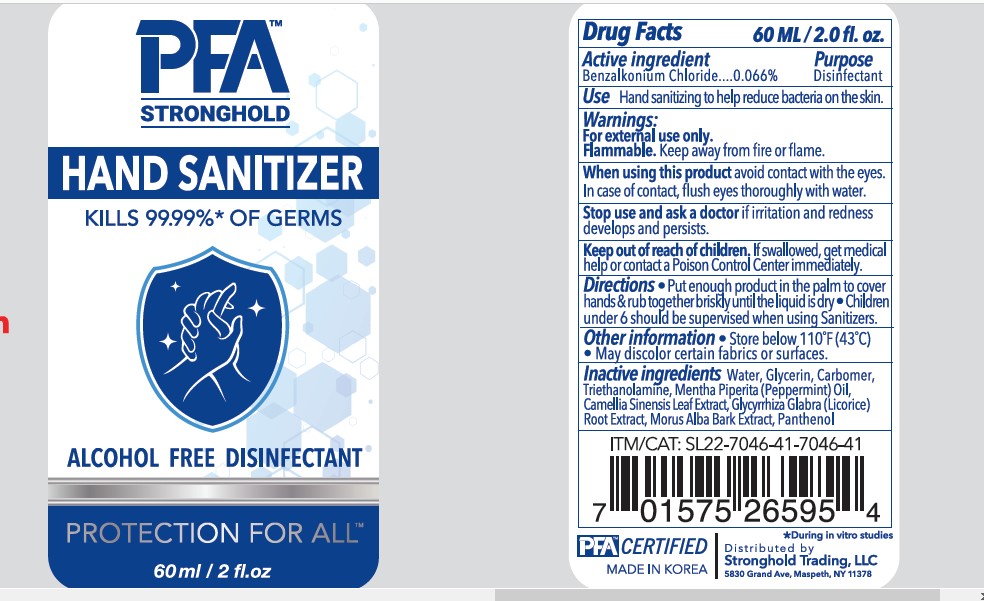 DRUG LABEL: PFA STRONGHOLD HAND SANITIZER
NDC: 80969-001 | Form: GEL
Manufacturer: STRONGHOLD TRADING LLC
Category: otc | Type: HUMAN OTC DRUG LABEL
Date: 20210813

ACTIVE INGREDIENTS: BENZALKONIUM CHLORIDE 0.066 g/100 mL
INACTIVE INGREDIENTS: GLYCERIN; TROLAMINE; PEPPERMINT OIL; MORUS ALBA BARK; PANTHENOL; WATER; CARBOMER COPOLYMER TYPE A (ALLYL PENTAERYTHRITOL CROSSLINKED); GREEN TEA LEAF; GLYCYRRHIZA GLABRA

80969-001-01 PFA HAND SANITIZER

Active ingredient

Benzalkonium Chloride 0.066%

Purpose

Disinfectant

Use

Hand sanitizing to help reduce bacteria on the skin.

Warnings

For external use only.

Flammable. Keep away from fire or flame.

When using this product, avoid contact with the eyes.

In case of contact, flush eyes thoroughly with water.

Stop use and ask a doctor if irritation and redness develops and persists.

Keep out of reach of children.

If swallowed, get medical help or contact a Poison Control Center immediately.

Directions

- Put enough product in the palm to cover hands & rub together briskly the liquid is dry.
- Children under 6 should be supervised when using Sanitizers.

Other information

- Store below 110°F (43°C)
- May discolor certain fabrics or surfaces.

Inactive ingredients

Water, Glycerin, Carbomer, Triethanolamine, Mentha Piperita (Peppermint) Oil, Camellia Sinensis Leaf Extract, Glycyrrhiza Glabra (Licorice) Root Extract, Morus Alba Bark Extract, Panthenol